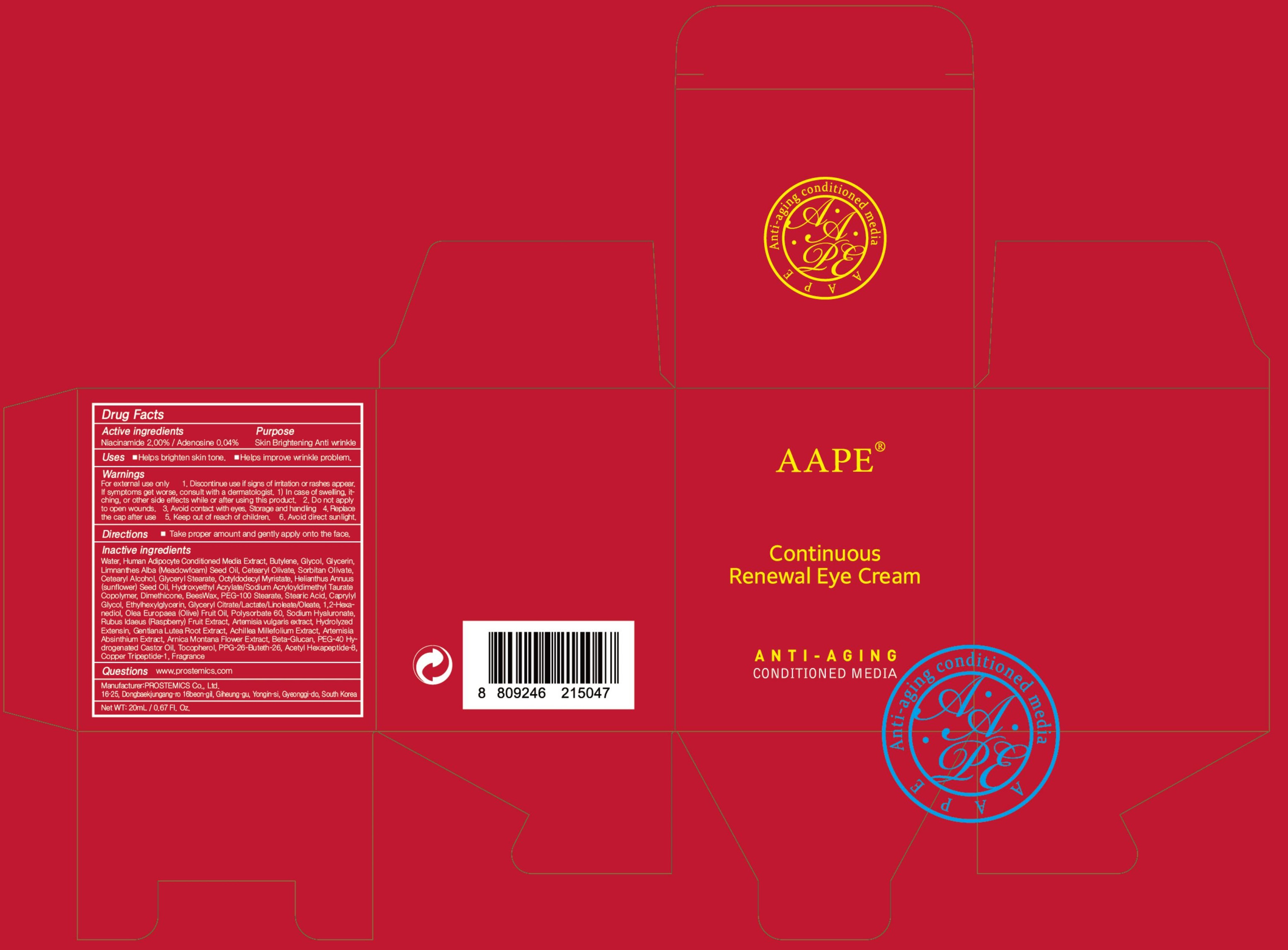 DRUG LABEL: AAPE Continuous Renewal Eye
NDC: 62041-230 | Form: CREAM
Manufacturer: PROSTEMICS Co., Ltd.
Category: otc | Type: HUMAN OTC DRUG LABEL
Date: 20190826

ACTIVE INGREDIENTS: Niacinamide 0.40 g/20 mL; Adenosine 0.008 g/20 mL
INACTIVE INGREDIENTS: Water; Butylene Glycol

ACTIVE INGREDIENT

Active ingredients: Niacinamide 2.00%, Adenosine 0.04%

INACTIVE INGREDIENT

Inactive ingredients:
Water, Human Adipocyte Conditioned Media Extract, Butylene Glycol, Glycerin, Limnanthes Alba (Meadowfoam) Seed Oil, Cetearyl Olivate, Sorbitan Olivate, Cetearyl Alcohol, Glyceryl Stearate, Octyldodecyl Myristate, Helianthus Annuus (sunflower) Seed Oil, Hydroxyethyl Acrylate/Sodium Acryloyldimethyl Taurate Copolymer, Dimethicone, BeesWax, PEG-100 Stearate, Stearic Acid, Caprylyl Glycol, Ethylhexylglycerin, Glyceryl Citrate/Lactate/Linoleate/Oleate, 1,2-Hexanediol, Olea Europaea (Olive) Fruit Oil, Polysorbate 60, Sodium Hyaluronate, Rubus Idaeus (Raspberry) Fruit Extract, Artemisia vulgaris extract, Hydrolyzed Extensin, Gentiana Lutea Root Extract, Achillea Millefolium Extract, Artemisia Absinthium Extract, Arnica Montana Flower Extract, Beta-Glucan, PEG-40 Hydrogenated Castor Oil, Tocopherol, PPG-26-Buteth-26, Acetyl Hexapeptide-8, Copper, Tripeptide-1, Fragrance

PURPOSE

Purpose: Skin Brightening, Anti wrinkle

WARNINGS

For external use only
1. Discontinue use if signs of irritation or rashes appear. If symptoms get worse, consult with a dermatologist. 1) In case of swelling, itching, or other side effects while or after using this product
2. Do not apply to open wounds.
3. Avoid contact with eyes.
Storage and handling
4. Replace the cap after use
5. Keep out of reach of children.
6. Avoid direct sunlight.

KEEP OUT OF REACH OF CHILDREN

Uses

Helps brighten skin tone.

Helps improve wrinkle problem.

Directions

Take proper amount and gently apply on to the face.